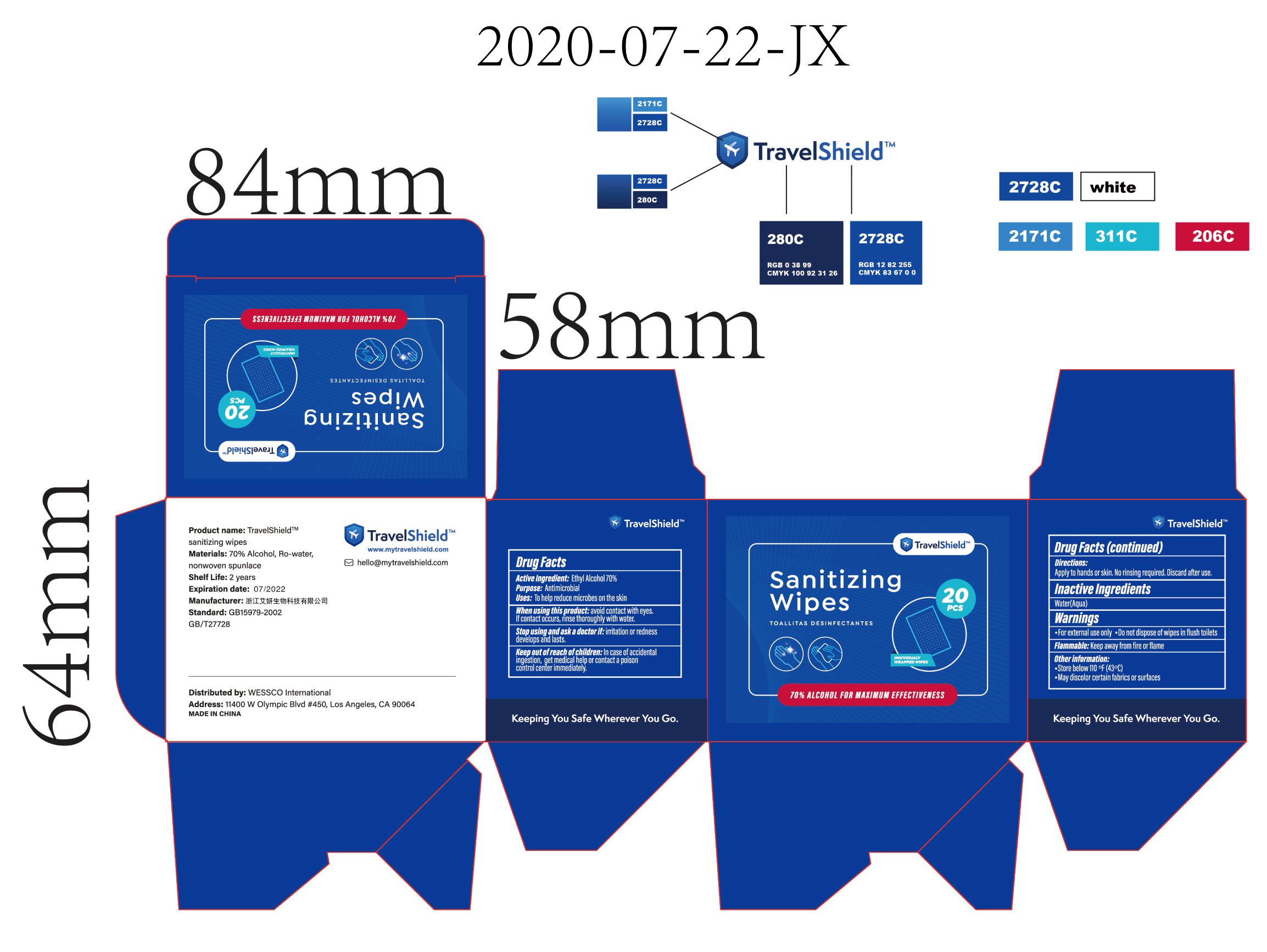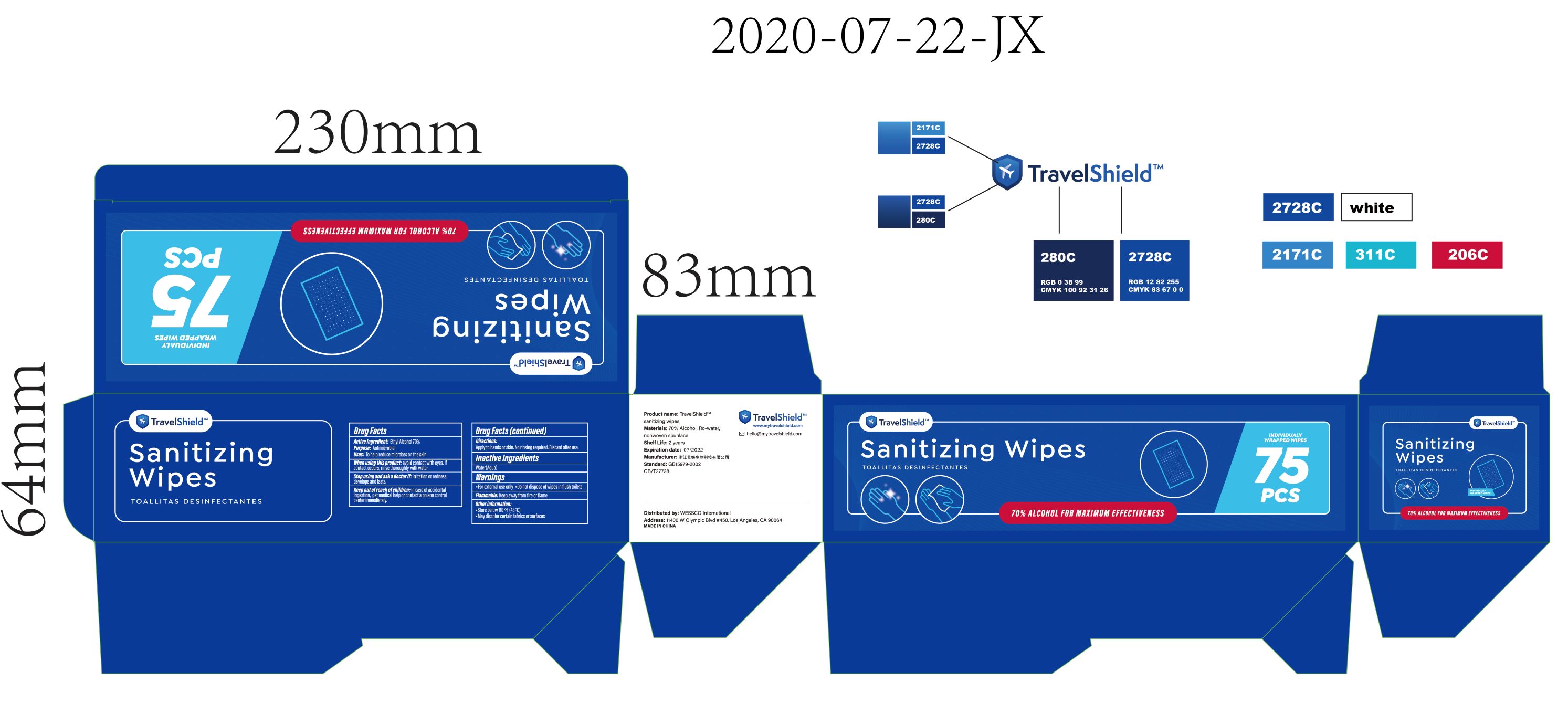 DRUG LABEL: Sanitizing Wipes
NDC: 74934-031 | Form: CLOTH
Manufacturer: Zhejiang iColor Biotech Co., Ltd
Category: otc | Type: HUMAN OTC DRUG LABEL
Date: 20200723

ACTIVE INGREDIENTS: ALCOHOL 70 mL/100 mL
INACTIVE INGREDIENTS: WATER

Zhejiang iColor Biotech Co., Ltd
Sanitizing Wipes 20pcs 75pcs

Active Ingredient(s)

Ethyl Alcohol 70% v/v.

Purpose

Antimicrobial

Use

To help reduce microbes on the skin.

Warnings

- For external use only.
- Do not dispose of wipes in flush toilets.
- Flammable: Keep away from fire or flame.

Do not use

- in children less than 2 months of age
- on open skin wounds

When using this product: avoid contact with eyes. lf contact occurs, rinse thoroughly with water.

STOP USE

Stop using and ask a doctor if: irritation or redness develops and lasts.

Keep out of reach of children: ln case of accidental ingestion, get medical help or contact a poison control center immediately.

Directions

Apply to hands or skin. No rinsing required. Discard after use.

Other information

- Store below 110 °F（43° C).
- May discolor certain fabrics or surfaces.

Inactive ingredients

Water(Aqua).

Package Label - Principal Display Panel

20pcs NDC: 74934-031-01

75pcs NDC: 74934-031-02